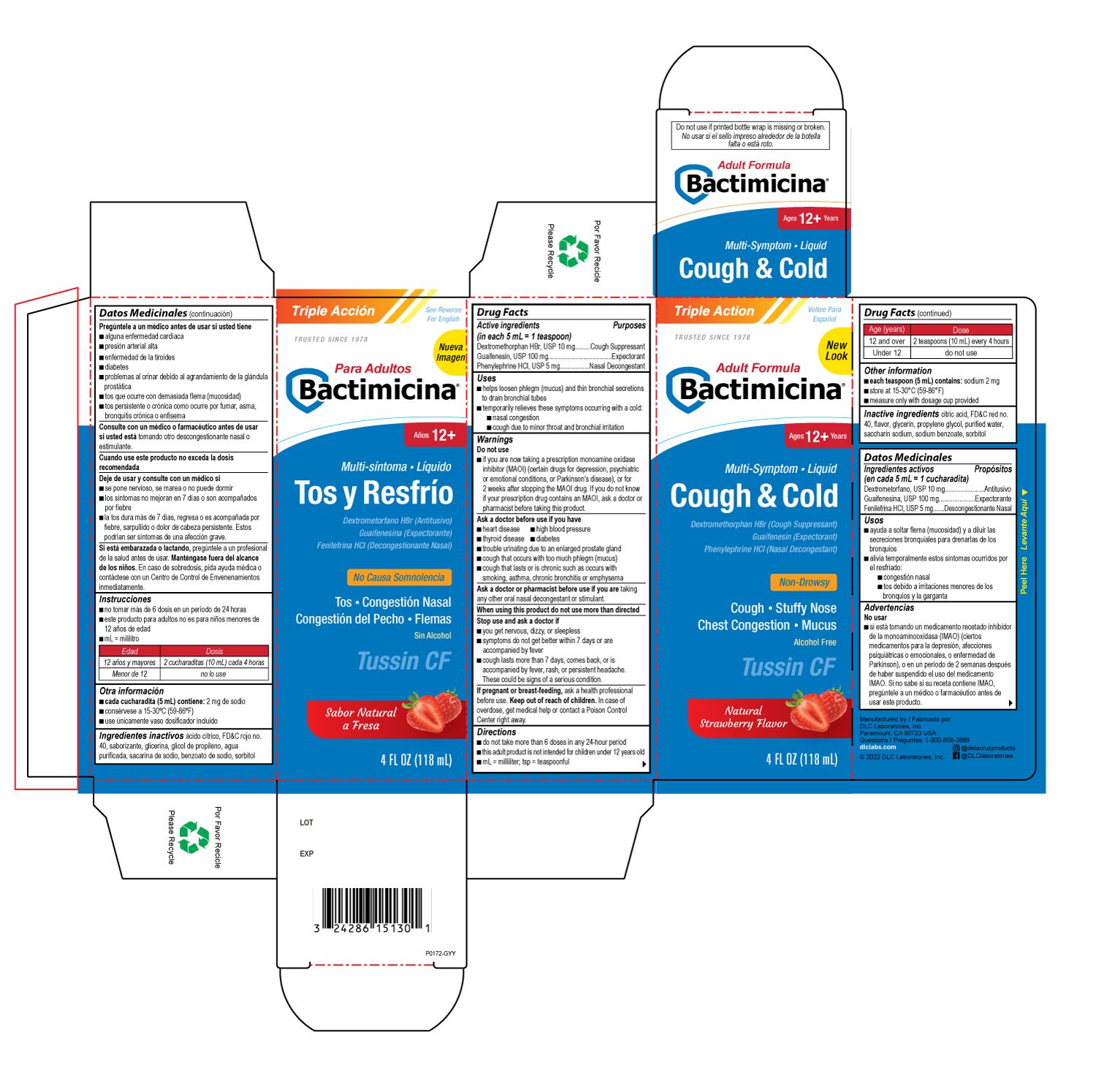 DRUG LABEL: BACTIMICINA COUGH AND COLD
NDC: 24286-1546 | Form: SOLUTION
Manufacturer: DLC Laboratories, Inc.
Category: otc | Type: HUMAN OTC DRUG LABEL
Date: 20260107

ACTIVE INGREDIENTS: DEXTROMETHORPHAN HYDROBROMIDE 10 mg/5 mL; GUAIFENESIN 100 mg/5 mL; PHENYLEPHRINE HYDROCHLORIDE 5 mg/5 mL
INACTIVE INGREDIENTS: CITRIC ACID MONOHYDRATE; FD&C RED NO. 40; PROPYLENE GLYCOL; WATER; SACCHARIN SODIUM; SODIUM BENZOATE; SORBITOL; GLYCERIN

BACTIMICINA® COUGH AND COLD

Drug Facts

ACTIVE INGREDIENT

PURPOSE

Active ingredients (in each 5 mL = 1 teaspoon) | Purposes
Dextromethorphan HBr, USP 10 mg | Cough Suppressant
Guaifenesin, USP 100 mg | Expectorant
Phenylephrine HCl, USP 5 mg | Nasal Decongestant

Uses

- helps loosen phlegm (mucus) and thin bronchial secretions to drain bronchial tubes
- temporarily relieves these symptoms occurring with a cold:
  - nasal congestion
  - cough due to minor throat and bronchial irritation

Warnings

Do not use

- if you are now taking a prescription monoamine oxidase inhibitor (MAOI) (certain drugs for depression, psychiatric or emotional conditions, or Parkinson's disease), or for 2 weeks after stopping the MAOI drug. If you do not know if your prescription drug contains an MAOI, ask a doctor or pharmacist before taking this product.

Ask a doctor before use if you have

- heart disease
- high blood pressure
- thyroid disease
- diabetes
- trouble urinating due to an enlarged prostate gland
- cough that occurs with too much phlegm (mucus)
- cough that lasts or is chronic such as occurs with smoking, asthma, chronic bronchitis or emphysema

Ask a doctor or pharmacist before use if you are taking any other oral nasal decongestant or stimulant.

When using this product do not use more than directed

Stop use and ask a doctor if

- you get nervous, dizzy, or sleepless
- symptoms do not get better within 7 days or are accompanied by fever
- cough lasts more than 7 days, comes back, or is accompanied by fever, rash, or persistent headache. These could be signs of a serious condition.

PREGNANCY OR BREAST FEEDING

If pregnant or breast-feeding, ask a health professional before use.

Keep out of reach of children. In case of overdose, get medical help or contact a Poison Control Center right away.

Directions

- do not take more than 6 doses in any 24-hour period
- this adult product is not intended for children under 12 years old
- mL=mililiter;tsp=teaspoonful

Age (years) | Dose
12 and over | 2 teaspoons (10 mL) every 4 hours
Under 12 | do not use

RECENT MAJOR CHANGES

mL=mililiter;tsp=teaspoonful

Other information

- each teaspoon (5 mL) contains: sodium 2 mg
- store at 15-30°C (59-86°F)
- measure only with dosage cup provided

Inactive ingredients

citric acid, FD&C red no. 40, flavor, glycerin, propylene glycol, purified water, saccharin sodium, sodium benzoate, sorbitol

Questions

1-800-858-3889

Manufactured by
DLC Laboratories, Inc.
Paramount, CA 90723 USA

Principal Display

Triple Action Voltee Para Esponol

TRUSTED SINCE 1978

New Look

Adult Formula

Bactimicina

Ages 12+ Years

Multi-Symptom • Liquid

Cough & Cold

Dextromethorphan HBr (Cough Suppresant)

Guaifenesin (Expectorant)

Phenylephrine HCl (Nasal Decongestant)

Non-Drowsy

Cough • Stuffy Nose

Chest Congestion • Mucus

Alcohol Free

Tussin CF

Natural Stawberry Flavor

4 FL OZ (118 mL)